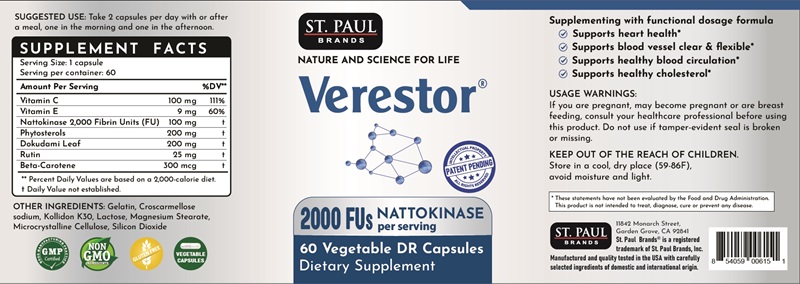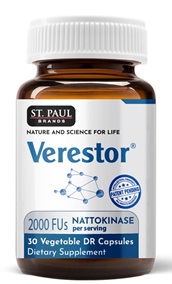 DRUG LABEL: St. Paul Brands Verestor
NDC: 13411-861 | Form: CAPSULE
Manufacturer: Advanced Pharmaceutical Services, Inc. Dba Affordable Quality Pharmaceuticals
Category: otc | Type: HUMAN OTC DRUG LABEL
Date: 20250331

ACTIVE INGREDIENTS: ASCORBIC ACID 100 mg/1 1; .ALPHA.-TOCOPHEROL 9 mg/1 1; NATTOKINASE 100 mg/1 1; .BETA.-SITOSTEROL 200 mg/1 1; HOUTTUYNIA CORDATA TOP 200 mg/1 1; RUTIN 25 mg/1 1; BETA CAROTENE 300 ug/1 1
INACTIVE INGREDIENTS: POVIDONE K30; LACTOSE, UNSPECIFIED FORM; CROSCARMELLOSE SODIUM; MICROCRYSTALLINE CELLULOSE; SILICON DIOXIDE; MAGNESIUM STEARATE

Identity

Dietary supplement

Warnings

If you are pregnant, may become pregnant or are breast feeding, consult your healthcare professional before using this product. Do not use if tamper-evident seal is broken or missing.

Direction

Take 2 capsules per day with or after a meal, one in the morning and one in the afternoon.

Safe handling warning

Store in a cool, dry place (59oF-86oF), avoid moisture and light.

HEALTH CLAIM

Supplementing with functional dosage formula

- Supports heart health*
- Supports blood vessel clear and flexible*
- Supports healthy blood circulation*
- Supports healthy cholesterol*

* These statements have not been evaluated by the Food & Drug Administration. This product is not intended to diagnose, treat, cure, or prevent any disease.

Other Ingredients

Gelatin, Croscarmellose sodium, kollidon K30, lactose, magnesium stearate, microcrystalline cellulose, silicondioxide